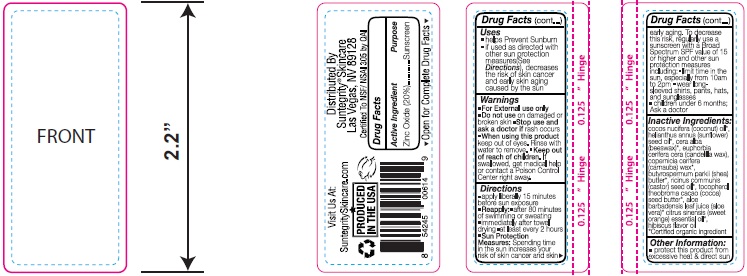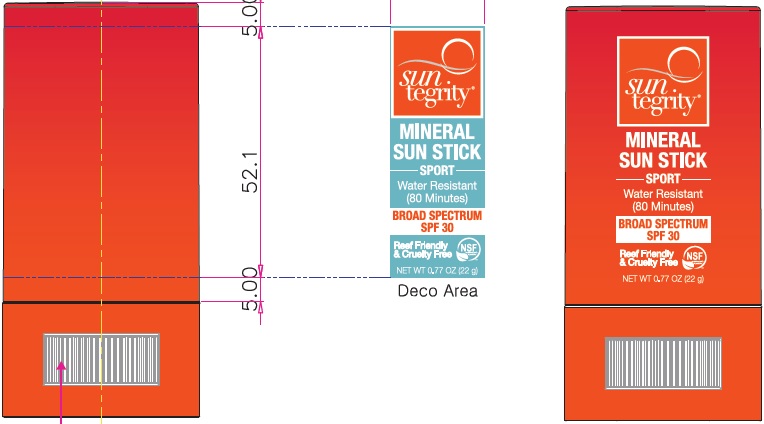 DRUG LABEL: SUNSCREEN
NDC: 62932-173 | Form: STICK
Manufacturer: Private Label Select Ltd CO
Category: otc | Type: HUMAN OTC DRUG LABEL
Date: 20200715

ACTIVE INGREDIENTS: ZINC OXIDE 22 g/100 g
INACTIVE INGREDIENTS: .BETA.-CITRONELLOL, (+/-)-; SUNFLOWER OIL; WHITE WAX; SHEA BUTTER; ALOE VERA LEAF; COCONUT OIL; GERANIOL; CITRUS SINENSIS FLOWER OIL; TOCOPHEROL; CANDELILLA WAX; CARNAUBA WAX; CASTOR OIL; COCOA BUTTER; LINALOOL, (+/-)-

Suntegrity Mineral Sunstick SPF30 22 gram